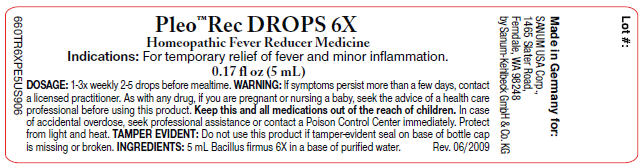 DRUG LABEL: Pleo Rec
NDC: 60681-3101 | Form: SOLUTION/ DROPS
Manufacturer: Sanum Kehlbeck GmbH & Co. KG
Category: homeopathic | Type: HUMAN OTC DRUG LABEL
Date: 20090930

ACTIVE INGREDIENTS: BACILLUS FIRMUS 6 [hp_X]/5 mL
INACTIVE INGREDIENTS: water

Pleo™ Rec
DROPS 6X

Homeopathic Fever Reducer Medicine

0.17 fl oz
(5 mL)

Indications

For temporary relief of fever and minor inflammation.

INGREDIENTS

5 mL Bacillus firmus 6X in a base of purified water.

Tamper Evident

Do not use this product if tamper-evident seal on base of bottle cap is missing or broken or if imprinted security strip on carton is torn.

DOSAGE

2–5 drops, 1–3 times weekly before mealtime.

WARNING

If symptoms persist more than a few days, contact a licensed practitioner. As with any drug, if you are pregnant or nursing a baby, seek the advice of a health care professional before using this product.

KEEP OUT OF REACH OF CHILDREN

Keep this and all medications out of the reach of children. In case of accidental overdose, seek professional assistance or contact a Poison Control Center immediately.

STORAGE AND HANDLING

Protect from light and heat.

Made in Germany

Distributed by:
SANUM USA Corp.
1465 Slater Road
Ferndale, WA 98248

Manufactured By:
Sanum-Kehlbeck,
GmbH & Co. KG

Rev. 05/2006

PRINCIPAL DISPLAY PANEL - 5 mL Label

Pleo™ Rec DROPS 6X

Homeopathic Fever Reducer Medicine

Indications: For temporary relief of fever and minor inflammation.

0.17 fl oz (5 mL)

DOSAGE: 1-3x weekly 2-5 drops before mealtime. WARNING: If symptoms persist more than a few days, contact
a licensed practitioner. As with any drug, if you are pregnant or nursing a baby, seek the advice of a health care
professional before using this product. Keep this and all medications out of reach of children. In case
of accidental overdose, seek professional assistance or contact a Poison Control Center immediately. Protect
from light and heat. TAMPER EVIDENT: Do not use this product if tamper-evident seal on base of bottle cap
is missing or broken. INGREDIENTS: 5 mL Bacillus firmus 6X in a base of purified water.
Rev. 06/2009